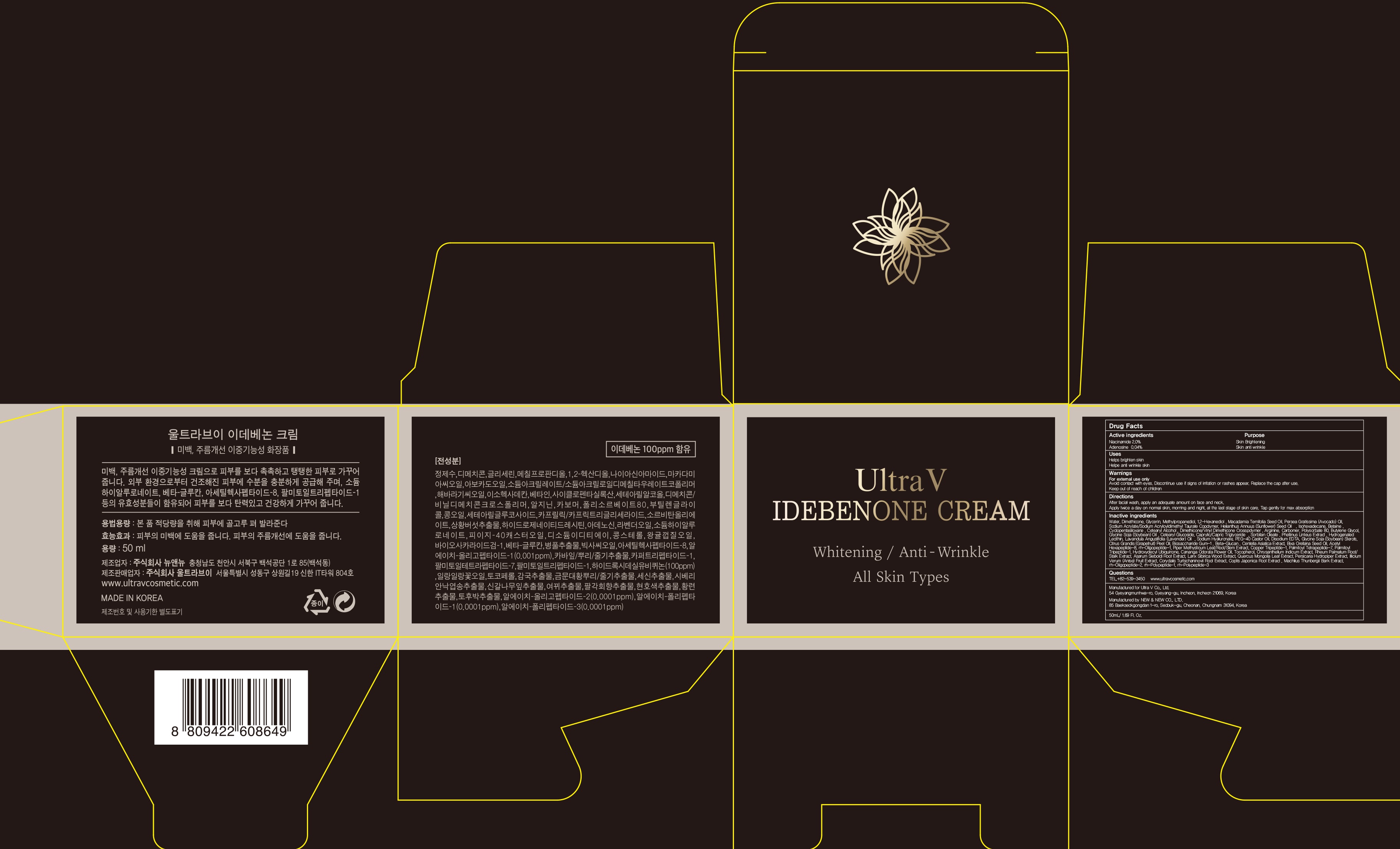 DRUG LABEL: Ultra V IDEBANONE
NDC: 71975-040 | Form: CREAM
Manufacturer: Ultra V Co., Ltd
Category: otc | Type: HUMAN OTC DRUG LABEL
Date: 20200401

ACTIVE INGREDIENTS: Niacinamide 1.0 g/50 mL; Adenosine 0.02 g/50 mL
INACTIVE INGREDIENTS: Water; Dimethicone

ACTIVE INGREDIENT

Active ingredients: Niacinamide 2.0%, Adenosine 0.04%

INACTIVE INGREDIENT

Inactive ingredients: Water, Dimethicone, Glycerin, Methylpropanediol, 1,2-Hexanediol , Macadamia Ternifolia Seed Oil, Persea Gratissima (Avocado) Oil, Sodium Acrylate/Sodium Acryloyldimethyl Taurate Copolymer , Helianthus Annuus (Sunflower) Seed Oil , Isohexadecane, Betaine , Cyclopentasiloxane , Cetearyl Alcohol , Dimethicone/Vinyl Dimethicone Crosspolymer , Arginine, Carbomer , Polysorbate 80, Butylene Glycol , Glycine Soja (Soybean) Oil , Cetearyl Glucoside, Caprylic/Capric Triglyceride , Sorbitan Oleate , Phellinus Linteus Extract , Hydrogenated Lecithin, Lavandula Angustifolia (Lavender) Oil , Sodium Hyaluronate, PEG-40 Castor Oil, Disodium EDTA, Glycine Soja (Soybean) Sterols , Citrus Grandis (Grapefruit) Peel Oil, Biosaccharide Gum-1 , Beta-Glucan , Centella Asiatica Extract, Bixa Orellana Seed Oil, Acetyl Hexapeptide-8, rh-Oligopeptide-1, Piper Methysticum Leaf/Root/Stem Extract, Copper Tripeptide-1, Palmitoyl Tetrapeptide-7, Palmitoyl Tripeptide-1, Hydroxydecyl Ubiquinone, Cananga Odorata Flower Oil, Tocopherol, Chrysanthellum Indicum Extract, Rheum Palmatum Root/Stalk Extract, Asarum Sieboldi Root Extract, Larix Sibirica Wood Extract, Quercus Mongolia Leaf Extract, Persicaria Hydropiper Extract, Illicium Verum (Anise) Fruit Extract, Corydalis Turtschaninovii Root Extract, Coptis Japonica Root Extract , Machilus Thunbergii Bark Extract, rh-Oligopeptide-2, rh-Polypeptide-1, rh-Polypeptide-3

PURPOSE

Purpose: Skin Brightening, Skin anti wrinkle

WARNINGS

Warnings: For external use only. Avoid contact with eyes. Discontinue use if signs of irritation or rashes appear. Replace the cap after use. Keep out of reach of children.

KEEP OUT OF REACH OF CHILDREN

Uses

Helps brighten skin

Helps anti wrinkle

Directions

Directions: After facial wash, apply an adequate amount on face and neck. Apply twice a day on normal skin, morning and night, at the last stage of skin care. Tap gently for max absorption

QUESTIONS

TEL,+82-539-3450

www.ultravcosmetic.com